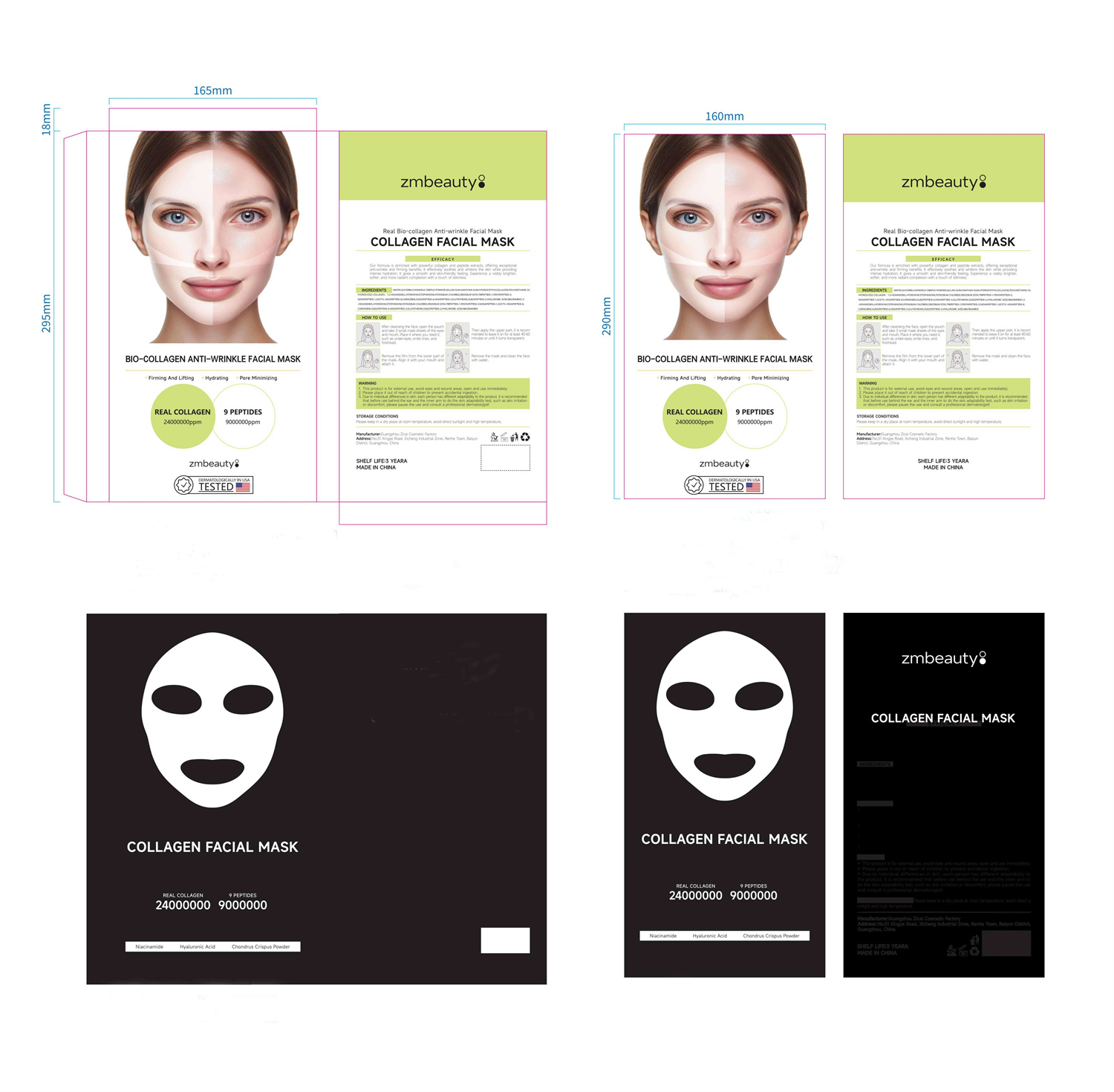 DRUG LABEL: Collagen Facial mask
NDC: 84716-109 | Form: DRESSING
Manufacturer: Shenzhen Boyang E-commerce Co.
Category: otc | Type: HUMAN OTC DRUG LABEL
Date: 20241104

ACTIVE INGREDIENTS: TRIPEPTIDE-1 0.136 g/136 g; 1,2-HEXANEDIOL 0.68 g/136 g; GLYCERIN 6.8 g/136 g
INACTIVE INGREDIENTS: WATER 118.932 g/136 g

ACTIVE INGREDIENTS

GLYCERIN 5%
HYDROLYZED COLLAGEN 1%
1,2-HEXANEDIOL 0.5%
HYDROXYACETOPHENONE 0.5%
POTASSIUM CHLORIDE 0.1%

PURPOSE

Our formula is enriched with powerful collagen and peptide extracts, offering exceptional anti-wrinkle and firming benefits, it effectively soothes and whitens the skin while providing intense hydration. lt gives a smooth and skin-friendly feeling. Experience a visibly brighter,softer,and more radiant complexion with a touch of silkiness.

Uses

1.After cieansing the face, open the pouch and take 3 small mask sheets of the eyes and mouth, Piace it where you need it,such as under-eyes, smile lines, and forehead.
2.Appiy the upper part of the mask,Align it with your eyes, and attach it.
3.Then apply the lower part, aligt it with your mouth,and attach it.It is recommended to leave it on for at least 40-60 minutes or untl it turns transparent.
4.Remove the mask and clean the face with water.

Warnings

1. This product is for external use, avoid eyes and wound areas, open and use immediately;

2. Please place it out of reach of children to prevent accidental ingestion.

3. Due to individual differences in skin, each person has different adaptability to the product, it is recommended that before use behind the ear and the inner arm to do the skin adaptability test, such as skin irritationor discomfort, please pause the use and consult a professional dermatologist.

Stop use and ask a doctor if

lt is recommended to have a skin test (inside the wrist orbehind the ear) before use.If you feel uncomfortable,please stop using it.

Do not use

on damaged or broken skin

Keep out of reach of children

Please place it out of the reach of infants；If swallowed, get medical help or contact a Poison Control Center right away.

When using this product

FOR EXTERNAL USE ONIY

keep out of eyes. Rinse with water to remove.

INACTIVE INGREDIENT SECTON

water

uses and storage method

1.After cieansing the face, open the pouch and take 3 small mask sheets of the eyes and mouth, Piace it where you need it,such as under-eyes, smile lines, and forehead.
2.Appiy the upper part of the mask,Align it with your eyes, and attach it.
3.Then apply the lower part, aligt it with your mouth,and attach it.It is recommended to leave it on for at least 40-60 minutes or untl it turns transparent.
4.Remove the mask and clean the face with water.

STORAGE CONDITIONS
Please keep in a dry place at room temperature, avoid direct sunlight and high temperature.